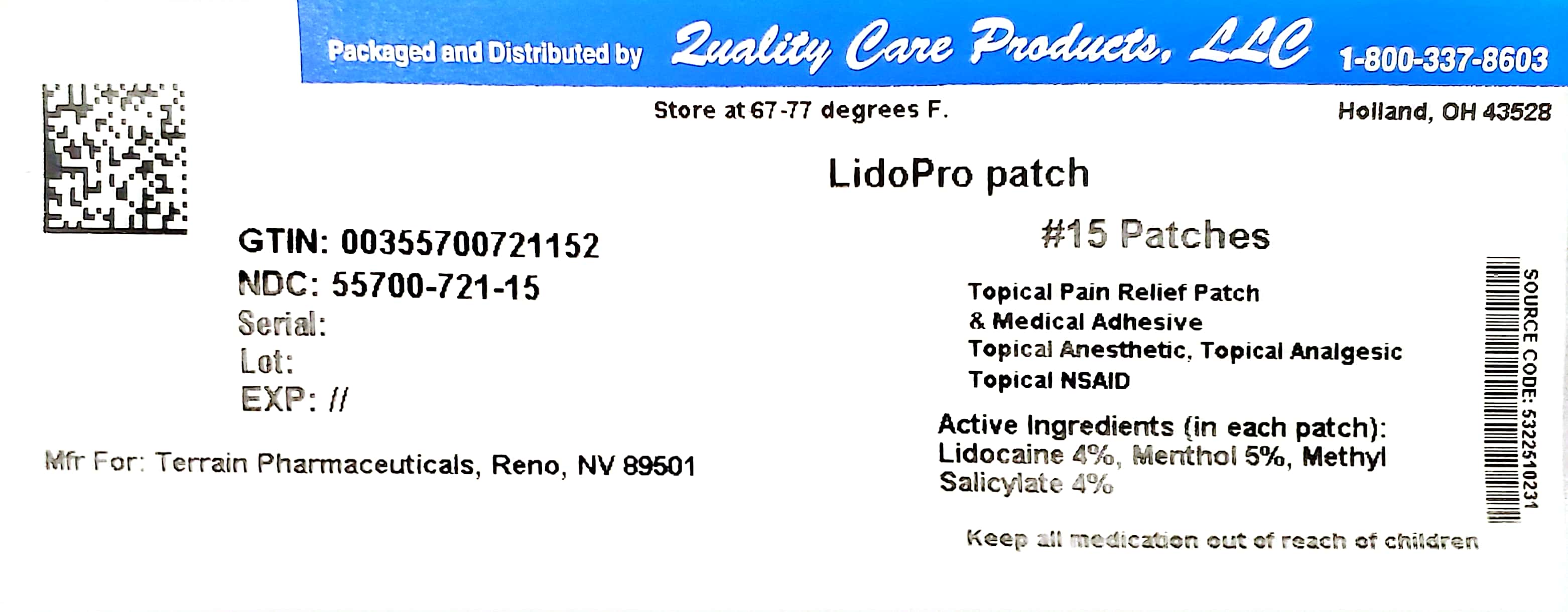 DRUG LABEL: LidoPro Patch
NDC: 55700-721 | Form: PATCH
Manufacturer: Quality Care Products, LLC
Category: otc | Type: HUMAN OTC DRUG LABEL
Date: 20231221

ACTIVE INGREDIENTS: LIDOCAINE HYDROCHLORIDE 4 mg/100 mg; MENTHOL 5 mg/100 mg; METHYL SALICYLATE 4 mg/100 mg
INACTIVE INGREDIENTS: ALUMINUM HYDROXIDE; CARBOXYMETHYLCELLULOSE SODIUM; 2-ETHYLHEXYL ACRYLATE; GLYCERIN; ISOPROPYL MYRISTATE; METHYL ACRYLATE; SODIUM POLYACRYLATE (8000 MW); NONOXYNOL-30; POLYACRYLIC ACID (250000 MW); POLYSORBATE 80; ACRYLIC ACID; SORBITAN SESQUIOLEATE; STARCH, CORN; TALC; TARTARIC ACID; TITANIUM DIOXIDE; WATER

LidoPro Patch

Active Ingredient

Lidocaine 4%

Purpose

Topical Analgesic

Active Ingredient

Menthol 5%

Purpose

Topical Analgesic

Active Ingredient

Methyl Salicylate 4%

Purpose

Topical Analgesic

Uses

Temporarily relieves mild to moderate aches and pains of muscles and joints associated with:

• muscle soreness

• strains

• sprains

• arthritis

• simple backache

• muscle stiffness

• bruises

Warnings

For external use only

Stomach bleeding warning

This product contains an NSAID, which may cause stomach bleeding. The chance is small, but higher if you

• are age 60 or older

• have had stomach ulcers or bleeding problems

• take other drugs containing an NSAID (Aspirin, Ibuprofen, Naproxen, or others)

• take a blood thinning (anticoagulant) or steroid drug

• have three or more alcoholic drinks every day while using this product

• take more or for a longer time than directed

Do not use

• on the face or rashes; on wounds or damaged skin

• in the eyes, mouth, or other mucous membranes

• on genitals

• with a heating pad

• if allergic to any NSAIDS

• right before or after heart surgery

• any patch from a pouch that has been opened for 7 or more days

Ask a doctor before use if

• you are allergic to topical products

• the stomach bleeding warning applies to you

• you are taking a diuretic

• you have high blood pressure, heart disease, or kidney disease

• you are pregnant

When using this product

• wash hands after applying or removing patch

• avoid contact with eyes. If eye contact occurs, rinse thoroughly with water

• the risk of heart attack or stroke may increase if you use more than directed or for longer than directed.

Stop use and consult your physician if

• stomach pain or upset gets worse or lasts

• rash, irritation, or itching develops

• you feel faint, vomit blood, or have bloody or black stools (these are signs of stomach bleeding)

• condition worsens

If pregnant or breast feeding,

ask a doctor before use while breast feeding and during the first 6 months of pregnancy. Do not use during last 3 months of pregnancy because it may cause problems in the unborn child or complications during delivery.

Keep out of reach of children.

If put in mouth, get medical help or contact a Poison Control Center right away. Package not child resistant. Dispose of the used patches by folding sticky ends together.

Directions

Adults 18 years and older:

• Apply patch to affected area 1 to 2 times daily or as directed.

Instructions for Use

• clean and dry affected area

• open pouch and remove one patch containing medical adhesive backing

• remove protective film from both patch and medical adhesive

• apply one patch to the affected area of pain and leave in place for 8 to 12 hours

• if pain lasts after using the first patch, a second patch may be applied for up to another 8 to 12 hours

• only use one patch at a time

• do not use more than 2 patches per day

• wash hands with soap and water after applying or removing patch

• reseal pouch containing unused patches after each use

Children under 18 years of age: Do not use

Other information

• some individuals may not experience pain relief until several minutes or hours after applying the patch

• avoid storing product in direct sunlight

• protect product from excessive moisture

• store at 67-77°F (19-25°C)

INACTIVE INGREDIENT

Acrylic Acid, Aluminum Hydroxide, Carmellose Sodium, 2-Ethylhexyl Acrylate, Glycerin, Isopropyl Myristate, Methyl Acrylate, Nonoxynol-30, Polyacrylic Acid, Polysorbate 80, Sodium Polyacrylate, Sorbitan Sesquioleate, Starch, Talc, Tartaric Acid, Titanium Dioxide, Water

QUESTIONS

Manufactured For:

Terrain Pharmaceuticals

Reno, NV 89501

Formulated and Designed in Nevada

Assembled in China

Patent Pending

LidoProTM patch

For questions or comments, call

877-985-8377